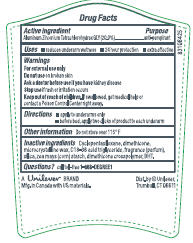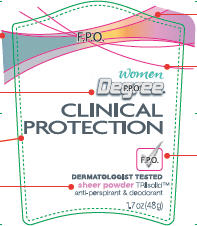 DRUG LABEL: Degree Clinical Protection Sheer Powder
NDC: 64942-1035 | Form: STICK
Manufacturer: Conopco Inc. d/b/a Unilever
Category: otc | Type: HUMAN OTC DRUG LABEL
Date: 20100608

ACTIVE INGREDIENTS: Aluminum Zirconium Tetrachlorohydrex GLY 20 g/100 g

PDP Degree Clinical Protection Sheer Powder IS AP and Deod., and drug facts

Active Ingredient Purpose

Aluminum Zirconium Tetrachlorohydrex GLY (20%).................anti-perspirant

Warnings For External Use only

INACTIVE INGREDIENT

Cyclopentasiloxane, Dimethicone, Microcrystalline Wax, C18-36 Acid Triglyceride, Fragrance (Parfum), Silica, Zea Mays (Corn) Starch, Dimethicone Crosspolymer, BHT.

Questions? Call toll-free 1-866-DEGREE1

Do not use on broken skin

Ask a doctor before use if you have kidney disease

Stop use if rash or irritation occurs

Keep out of reach of children. If swallowed, get medical help or contact a Poison Control Center right away.

PACKAGE LABEL

PDP front 1.7oz

PACKAGE LABEL

PDP 1.7 oz back